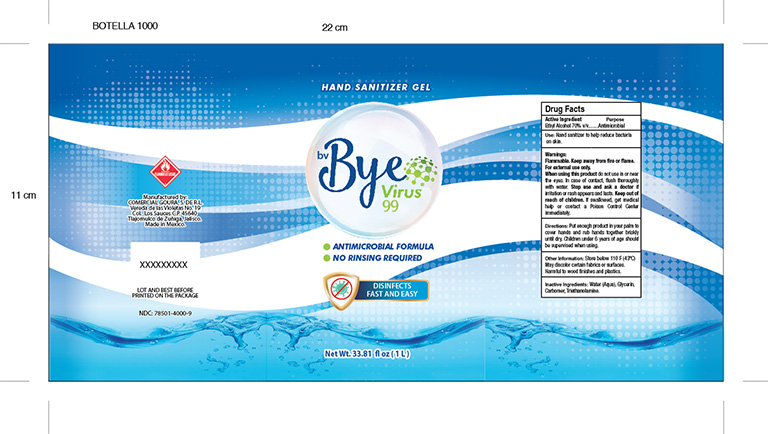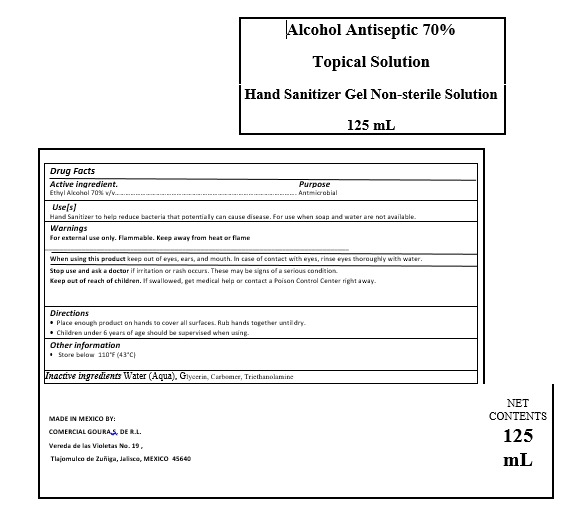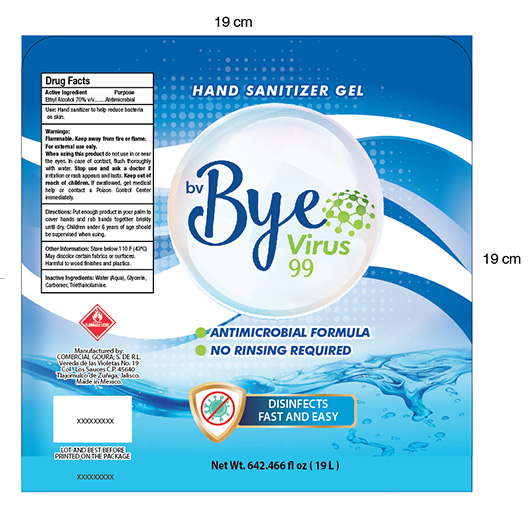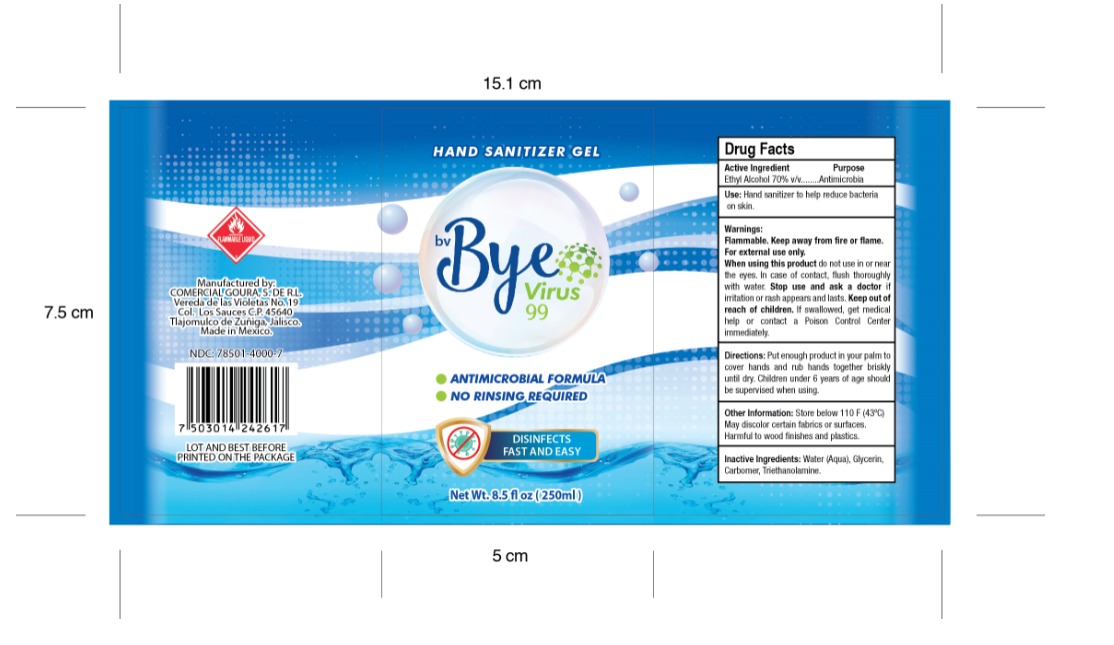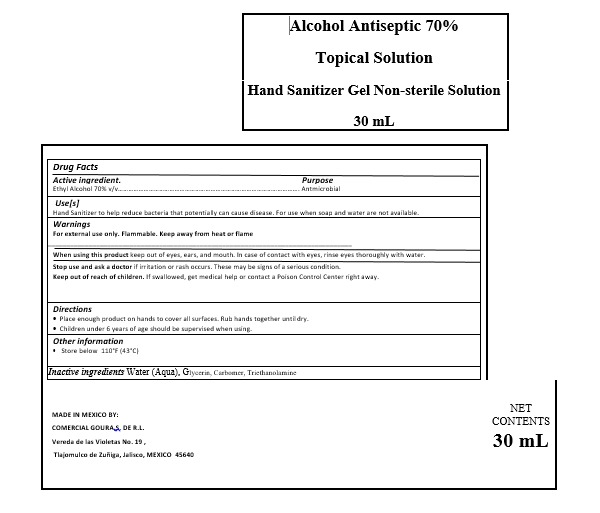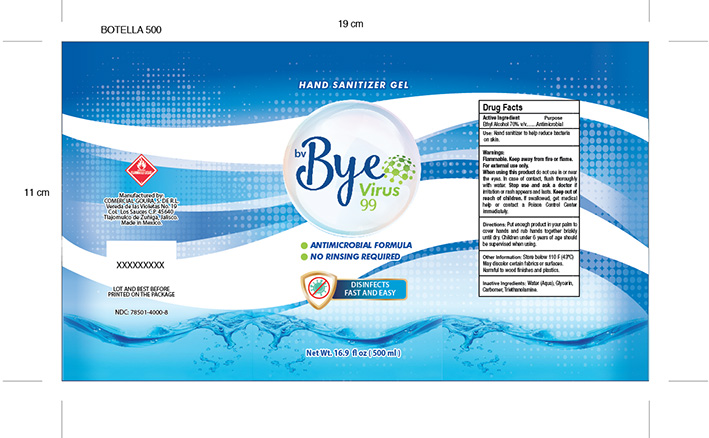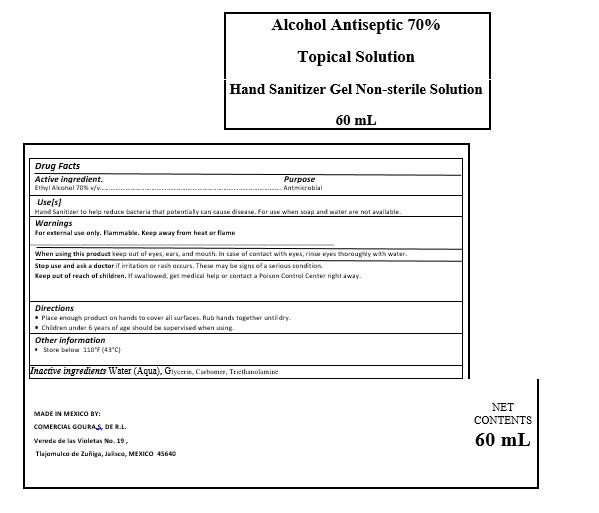 DRUG LABEL: BV BYE VIRUS 99
NDC: 78501-4000 | Form: GEL
Manufacturer: COMERCIAL GOURA,S. DE R.L.
Category: otc | Type: HUMAN OTC DRUG LABEL
Date: 20200713

ACTIVE INGREDIENTS: ALCOHOL 0.7 mL/1 mL
INACTIVE INGREDIENTS: WATER 0.2585 mL/1 mL; CARBOMER 940 0.002 mL/1 mL; TRIETHANOLAMINE CAPROYL GLUTAMATE 0.002 mL/1 mL; GLYCERIN 0.0375 mL/1 mL

BV BYE VIRUS HAND SANITIZER GEL

DOSAGE AND ADMINISTRATION

Directions

Place enough product on hands to cover all surfaces. Rub hands together until dry.

Children under 6 years of age should be supervised when using.

WARNINGS AND PRECAUTIONS

Store below 110°F (43°C)

Children under 6 years of age should be supervised when using.

WARNINGS

For external use only. Flammable. Keep away from heat or flame

ACTIVE INGREDIENT

Active ingredienT Ethyl Alcohol 70% v/v…

INACTIVE INGREDIENTS

Water (Aqua), Glycerin, Carbomer, Triethanolamine

Keep out of reach of children. If swallowed, get medical help or contact a Poison Control Center right away

STOP USE

Stop use and ask a doctor if irritation or rash occurs. These may be signs of a serious condition.

PURPOSE

PURPOSE ANTIMICROBIAL

INDICATIONS AND USAGE

Use[s]

Hand Sanitizer to help reduce bacteria that potentially can cause disease. For use when soap and water are not available.